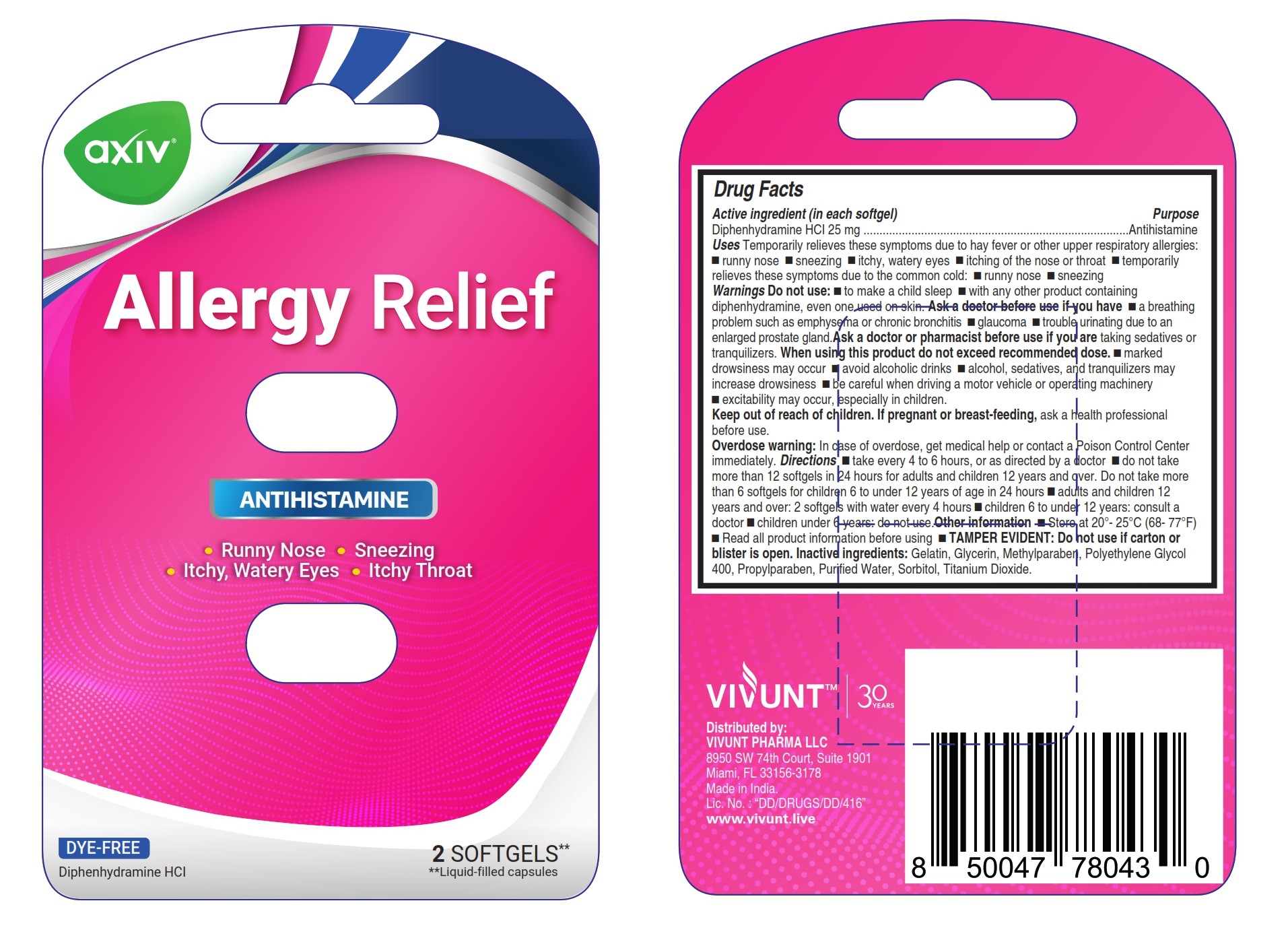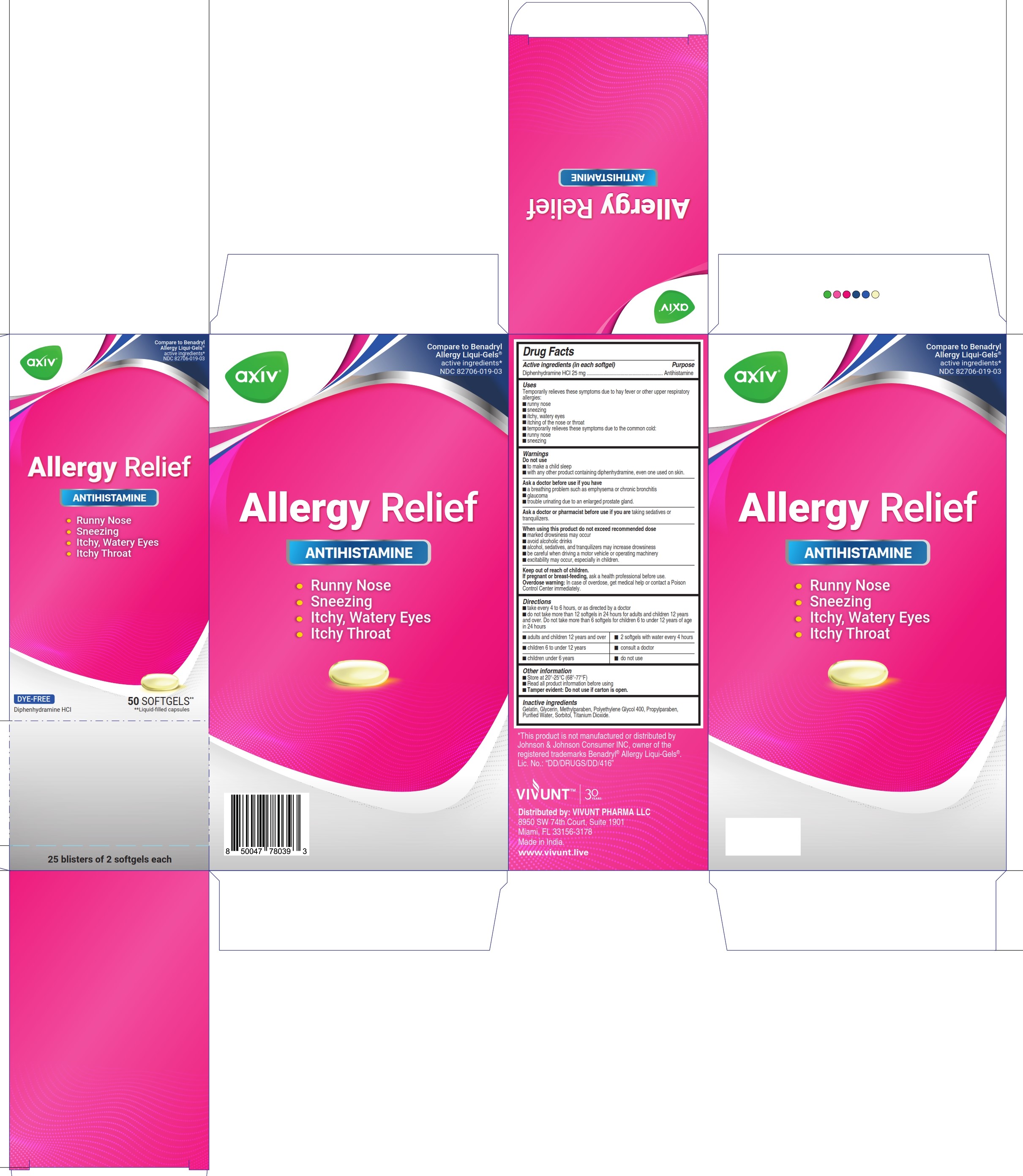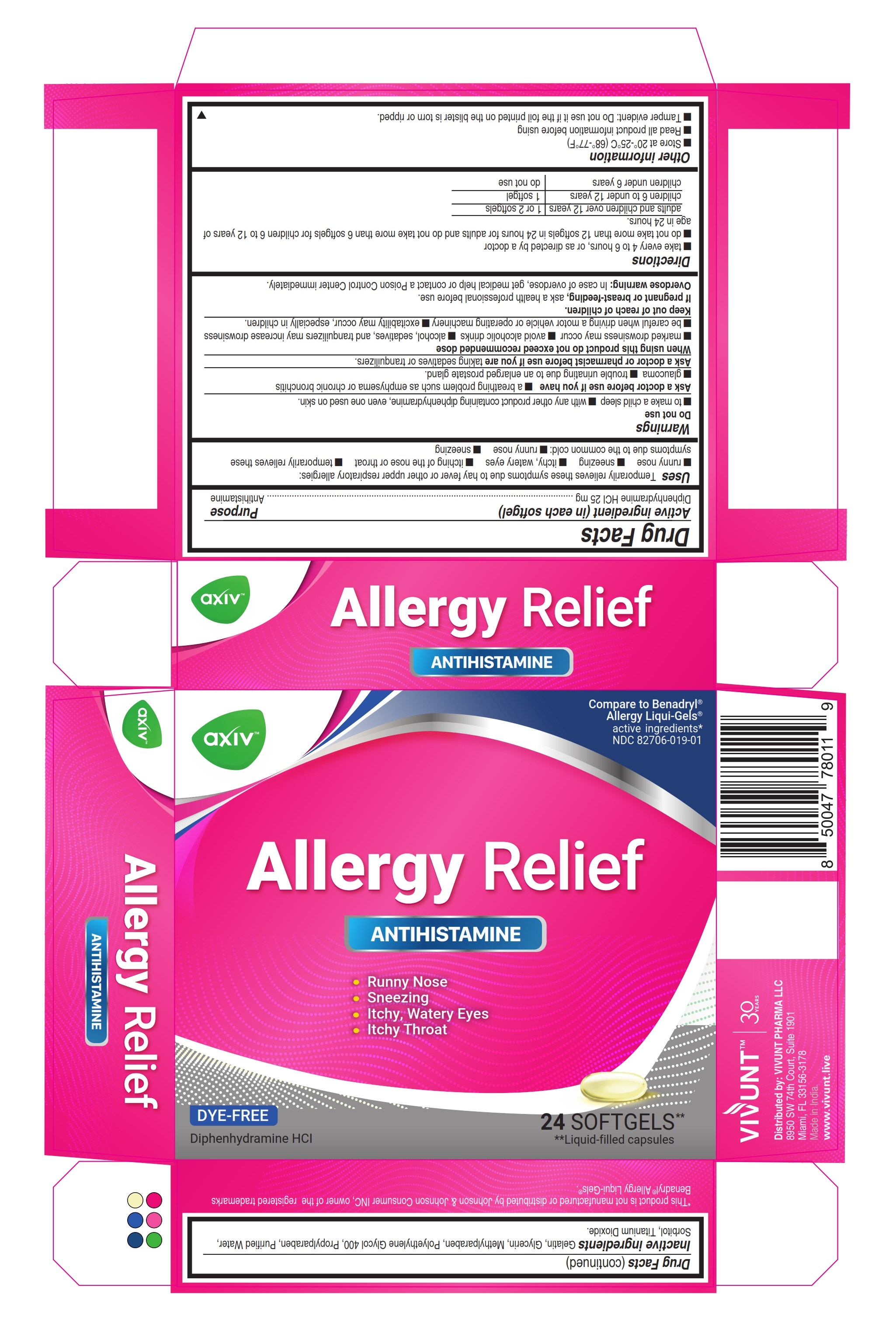 DRUG LABEL: AXIV Allergy
NDC: 82706-019 | Form: CAPSULE, LIQUID FILLED
Manufacturer: VIVUNT PHARMA LLC
Category: otc | Type: HUMAN OTC DRUG LABEL
Date: 20250917

ACTIVE INGREDIENTS: DIPHENHYDRAMINE HYDROCHLORIDE 25 mg/1 1
INACTIVE INGREDIENTS: PROPYLPARABEN; GELATIN; METHYLPARABEN; WATER; GLYCERIN; SORBITOL; POLYETHYLENE GLYCOL 400; TITANIUM DIOXIDE

AXIV Allergy Relief

Drug Facts

ACTIVE INGREDIENT

Active Ingredient (in each softgel) | Purpose
Diphenhydramine HCl 25 mg | Antihistamine

Uses

- temporarily relieves these symptoms due to hay fever or other upper respiratory allergies:
- runny nose
- sneezing
- itchy, watery eyes
- itching of the nose or throat
- temporarily relieves these symptoms due to the common cold:
- runny nose
- sneezing

Warnings

Do not use

- to make a child sleepy
- with any other product containing diphenhydramine, even one used on skin

Ask a doctor before use if you have

- a breathing problem such as emphysema or chronic bronchitis
- glaucoma
- trouble urinating due to an enlarged prostate gland

Ask a doctor or pharmacist before use if you are

taking sedatives or tranquilizers

When using this product

- marked drowsiness may occur
- avoid alcoholic drinks
- alcohol, sedatives, and tranquilizers may increase drowsiness
- be careful when driving a motor vehicle or operating machinery
- excitability may occur, especially in children

Keep out of reach of children

If pregnant or breast-feeding

ask a health professional before use.

Overdose Warning

In case of overdose, get medical help or contact a Poison Control Center immediately.

Directions

- Take every 4 to 6 hours, or as directed by a doctor
- Do not take more than 12 Softgels in 24 hours for Adults and children 12 years and over. Do not take more than 6 Softgels for children 6 to under 12 years of age in 24 hours.

adults and children 12 years and over | 1 or 2 Softgels
children 6 to under 12 years | 1 Softgel
children under 6 years | do not use

Other information

- Store at 20° - 25 °C (68 °- 77 °F)
- Read all product information before using
- Tamper Evident: Do not use if the foil printed on the blister is torn or ripped.
- Tamper Evident: Do not use if carton or pouch is open

Inactive ingredients

Gelatin, Glycerin, Methylparaben, Polyethylene Glycol 400, Propylparaben, Purified Water, Sorbitol, Titanium Dioxide

*This product is not manufactures or distributed by Johnson & Johnson Consumer INC, owner of the registered trademarks Benadryl® Allergy Liqui-Gels®

Distributed by: VIVUNT PHARMA LLC

8950 SW 74th Court, Suite 1901

Miami, FL 33156-3178

Made in India.

www.vivunt.live

PRINCIPAL DISPLAY PANEL 24

Compare to Benadryl® Allergy Liqui-Gels®

active ingredients*

NDC 82706-019-01

AXIV Antihistamine

- Runny Nose
- Sneezing
- Itchy, Watery Eyes
- Itchy Throat

DYE-FREE

Diphenhydramine HCl

24 SOFTGELS** **Liquid-filled capsules

Allergy Relief 50 softgels

Compare to Benadryl® Allergy Liqui-Gels®

active ingredients*

NDC 82706-019-03

AXIV Antihistamine

Runny Nose
Sneezing
Itchy, Watery Eyes
Itchy Throat

DYE-FREE

Diphenhydramine HCl

50 SOFTGELS** **Liquid-filled capsules